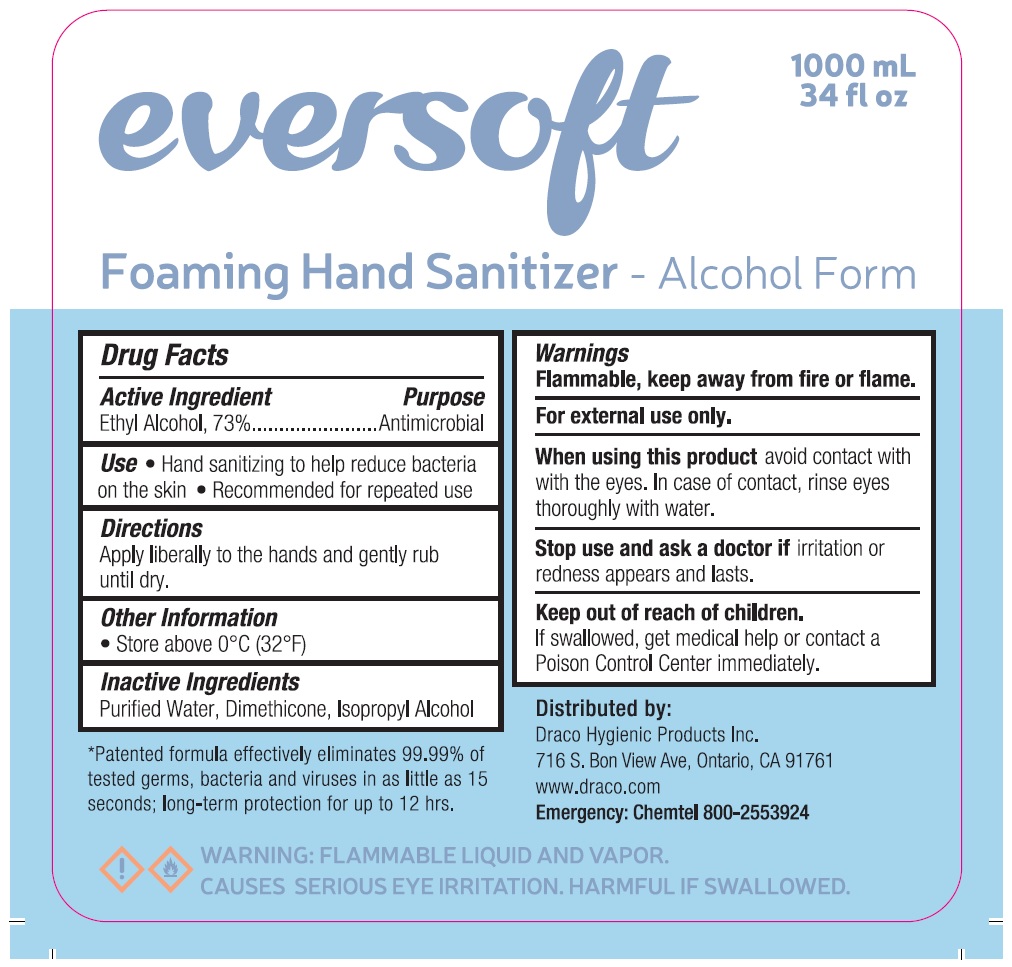 DRUG LABEL: Eversoft Foaming Hand Sanitizer
NDC: 78168-003 | Form: LIQUID
Manufacturer: Teh Tung Corporation
Category: otc | Type: HUMAN OTC DRUG LABEL
Date: 20201021

ACTIVE INGREDIENTS: ALCOHOL 73 mL/100 mL
INACTIVE INGREDIENTS: WATER; DIMETHICONE; ISOPROPYL ALCOHOL

eversoft Foaming Hand Sanitizer

Active Ingredient

Ethyl Alcohol, 73%

Purpose

Antimicrobial

Use

• Hand sanitizing to help reduce bacteria on the skin • Recommended for repeated use

Directions

Apply liberally to the hands and gently rub until dry.

Other Information

• Store above 0°C (32°F)

Inactive Ingredients

Purified Water, Dimethicone, Isopropyl Alcohol

Warnings

Flammable, keep away from fire or flame.

For external use only.

When using this product avoid contact with the eyes. In case of contact, rinse eyes thoroughly with water.

Stop use and ask a doctor if irritation or redness appears and lasts.

Keep out of reach of children. If swallowed, get medical help or contact a Poison Control Center immediately.

Foaming Hand Sanitizer - Alcohol Form

*Patented formula effectively eliminates 99.99% of tested germs, bacteria and viruses in as little as 15 seconds; long-term protection for up to 12 hrs.

Distributed by:

Draco Hygienic Products Inc.

716 S. Bon View Ave, Ontario, CA 91761

www.draco.com

Emergency: Chemtel 800-2553924

WARNING: FLAMMABLE LIQUID AND VAPOR.

CAUSES SERIOUS EYE IRRITATION. HARMFUL IF SWALLOWED.